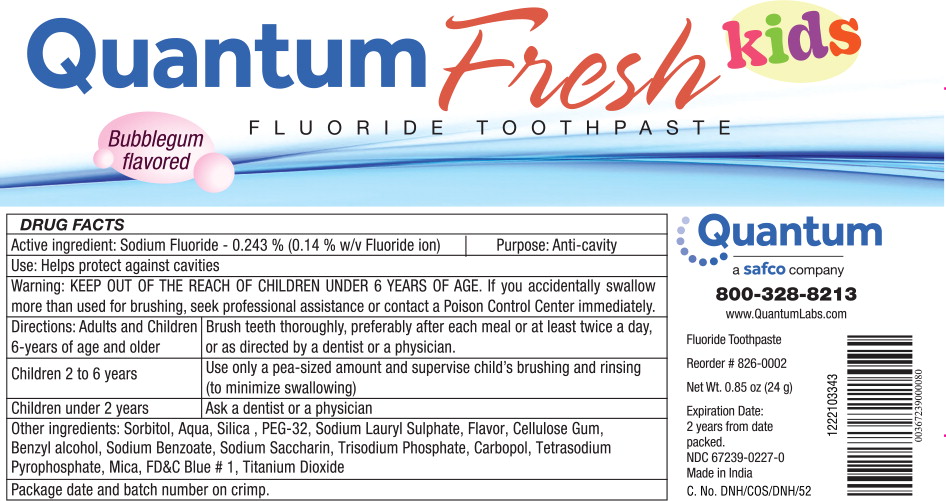 DRUG LABEL: Sodium Fluoride
NDC: 67239-0227 | Form: PASTE, DENTIFRICE
Manufacturer: Safco Dental Supply LLC
Category: otc | Type: HUMAN OTC DRUG LABEL
Date: 20231011

ACTIVE INGREDIENTS: SODIUM FLUORIDE 2.43 mg/1 g
INACTIVE INGREDIENTS: SORBITOL; SILICON DIOXIDE; WATER; GLYCERIN; POLYETHYLENE GLYCOL 1500; SODIUM LAURYL SULFATE; TITANIUM DIOXIDE; CARBOXYMETHYLCELLULOSE SODIUM; CARRAGEENAN; XANTHAN GUM; BUTYL ESTER OF METHYL VINYL ETHER/MALEIC ANHYDRIDE COPOLYMER (125000 MW); SODIUM PHOSPHATE, TRIBASIC, DODECAHYDRATE; SACCHARIN SODIUM; SODIUM PYROPHOSPHATE; SODIUM BENZOATE; METHYLPARABEN; PROPYLPARABEN; BENZYL ALCOHOL; TRICLOSAN; PROPYLENE GLYCOL; SODIUM HYDROXIDE; FD&C BLUE NO. 1; MICA; CARBOMER HOMOPOLYMER TYPE C (ALLYL PENTAERYTHRITOL CROSSLINKED)

DRUG FACTS

Active ingredient:

Sodium Fluoride - 0.243 % (0.14 % w/v Fluoride ion)

Purpose:

Anti-cavity

Use:

Helps protect against cavities

Warning:

KEEP OUT OF REACH OF CHILDREN

KEEP OUT OF THE REACH OF CHILDREN UNDER 6 YEARS OF AGE. If you accidentally swallow more than used for brushing, seek professional assistance or contact a Poison Control Center immediately.

Directions:

Adults and Children 6-years of age and older

Brush teeth thoroughly, preferably after each meal or at least twice a day, or as directed by a dentist or a physician.

Children 2 to 6 years

Use only a pea-sized amount and supervise child's brushing and rinsing (to minimize swallowing)

Children under 2 years

Ask a dentist or a physician

Other ingredients:

Sorbitol, Aqua, Silica, PEG-32, Sodium Lauryl Sulphate, Flavor, Cellulose Gum, Benzyl alcohol, Sodium Benzoate, Sodium Saccharin, Trisodium Phosphate, Carbopol, Tetrasodium Pyrophosphate, Mica, FD&C Blue # 1, Titanium Dioxide

Package date and batch number on crimp.

Principal Display Panel –

Quantum Fresh kids
FLUORIDE TOOTHPASTE

Bubblegum
flavored

Quantum
a safco company

800-328-8213

www.QuantumLabs.com

Fluoride Toothpaste

Reorder #826-0002

Net Wt. 0.85 oz (24 g)

Expiration Date:
2 years from date
packed.

NDC 67239-0227-0

Made in India

C. No. DNH/COS/DNH/52